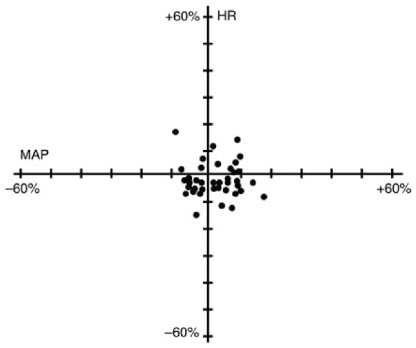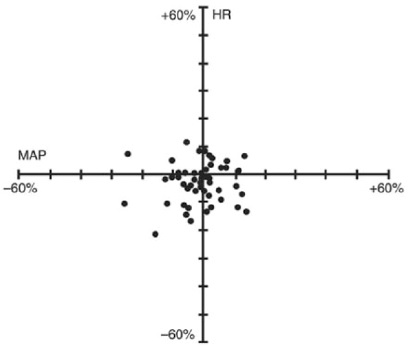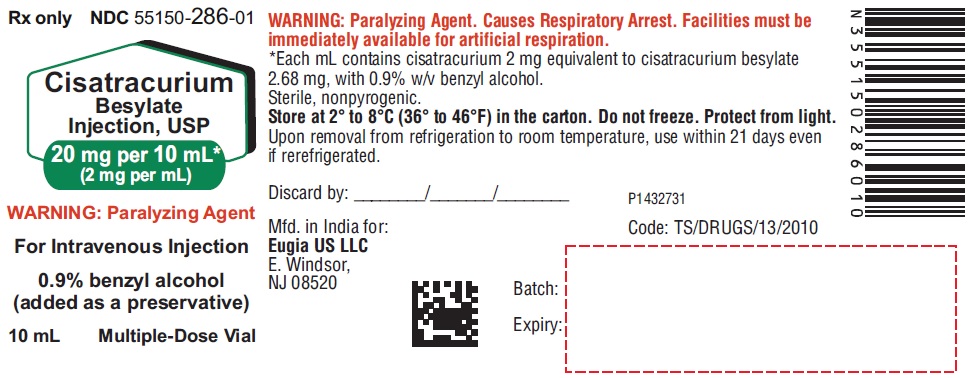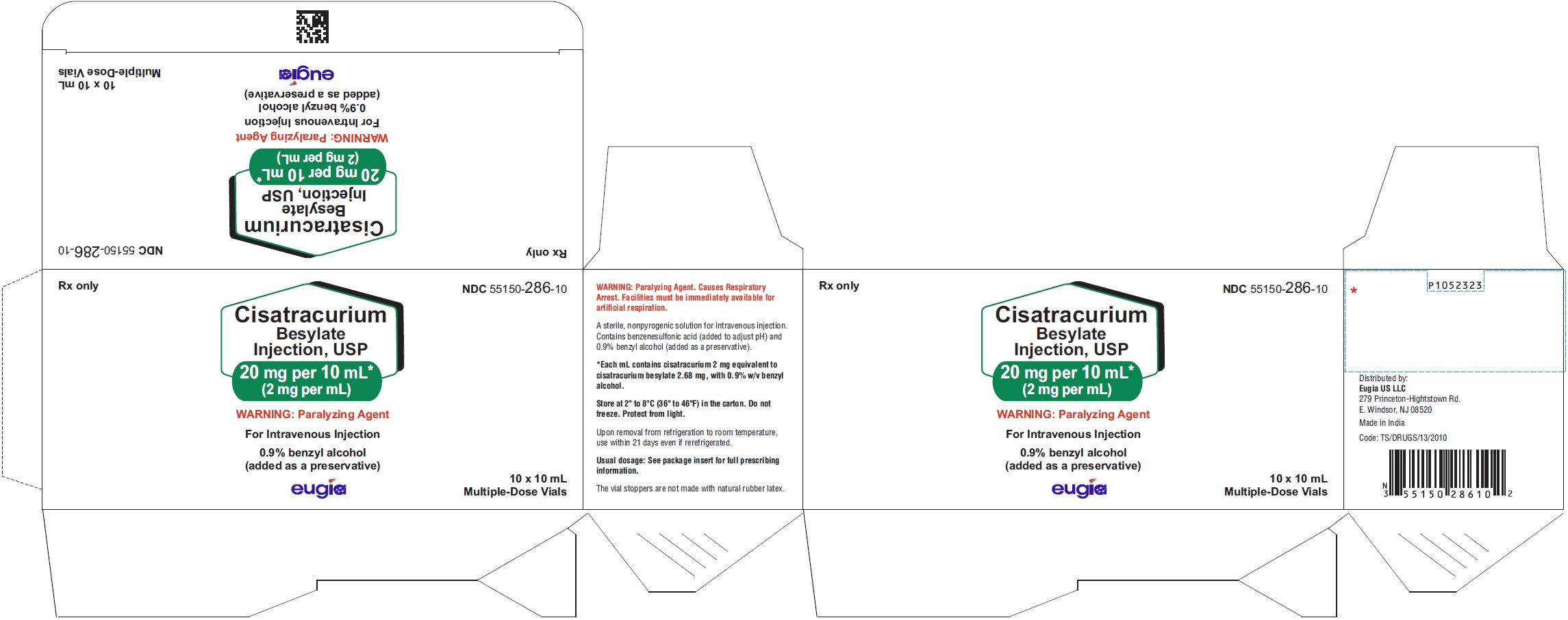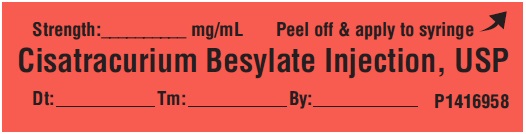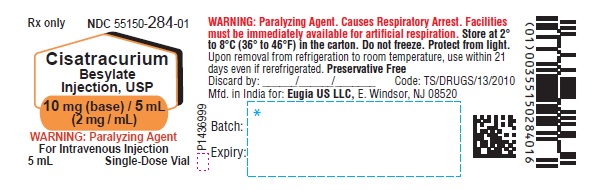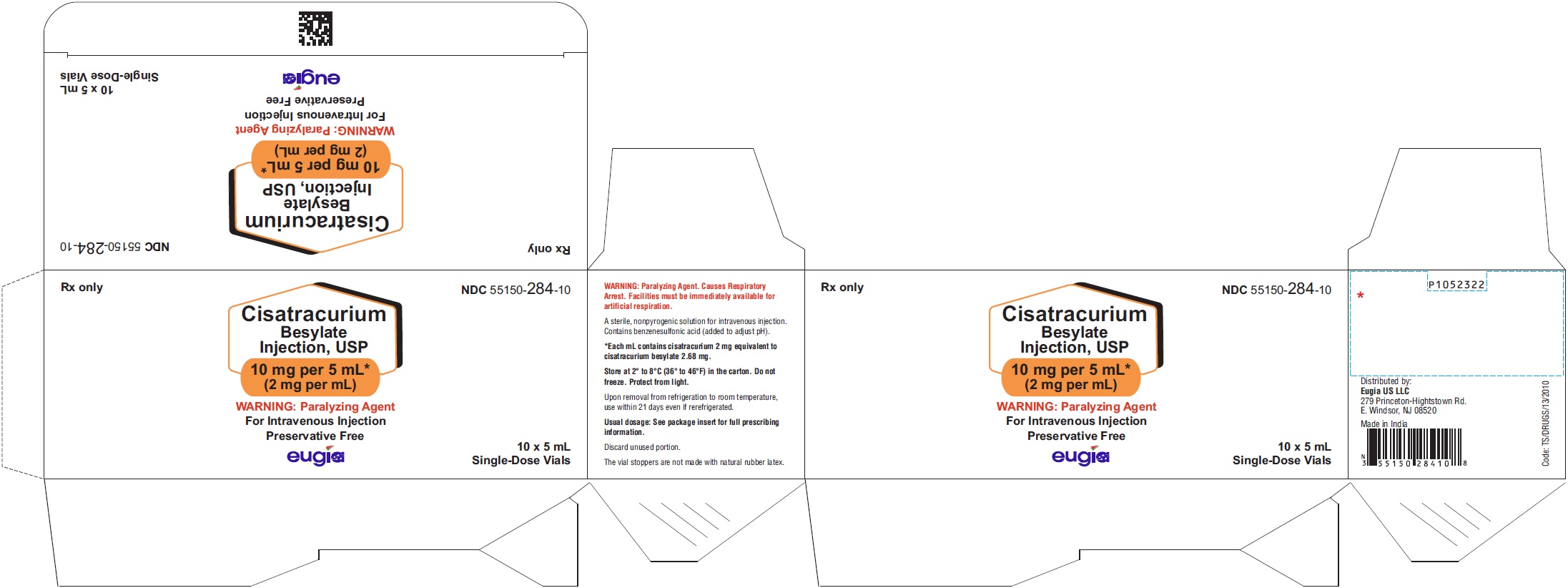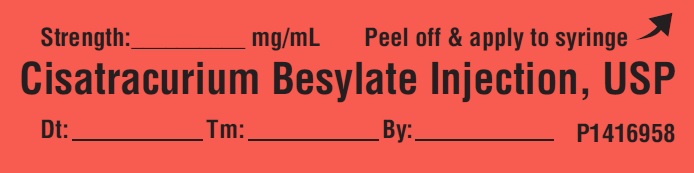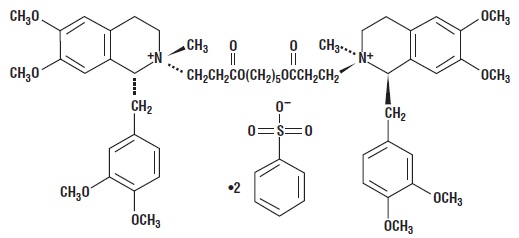 DRUG LABEL: Cisatracurium Besylate
NDC: 55150-286 | Form: INJECTION
Manufacturer: Eugia US LLC
Category: prescription | Type: Human Prescription Drug Label
Date: 20251107

ACTIVE INGREDIENTS: CISATRACURIUM BESYLATE 20 mg/10 mL
INACTIVE INGREDIENTS: BENZYL ALCOHOL; BENZENESULFONIC ACID; WATER

HIGHLIGHTS OF PRESCRIBING INFORMATION

These highlights do not include all the information needed to use CISATRACURIUM BESYLATE INJECTION safely and effectively. See full prescribing information for CISATRACURIUM BESYLATE INJECTION.
CISATRACURIUM BESYLATE injection, for intravenous use
Initial U.S. Approval: 1995

1 INDICATIONS AND USAGE

Cisatracurium besylate injection is a nondepolarizing neuromuscular blocker indicated:

- as an adjunct to general anesthesia to facilitate tracheal intubation in adults and in pediatric patients 1 month to 12 years of age (1)
- to provide skeletal muscle relaxation during surgery in adults and in pediatric patients 2 to 12 years of age as a bolus or infusion maintenance (1)
- for mechanical ventilation in the ICU in adults (1)

Limitations of Use:
Cisatracurium besylate injection is not recommended for rapid sequence endotracheal intubation due to the time required for its onset of action (1)

2 DOSAGE AND ADMINISTRATION

Store cisatracurium besylate injection with the cap and ferrule intact and in a manner that minimizes the possibility of selecting the wrong product (2.1)

- Administer intravenously only by or under the supervision of experienced clinicians familiar with drug’s actions and possible complications (2.1)
- Use only if personnel and facilities for resuscitation and life support, and a cisatracurium besylate injection antagonist are immediately available (2.1)
- Use a peripheral nerve stimulator to determine adequacy of blockade (e.g., need for additional doses), minimize risk of overdosage or underdosage, assess extent of recovery from blockade, potentially limit exposure to toxic metabolites through dose titration, and facilitate more rapid reversal of cisatracurium besylate injection-induced paralysis (2.1)
- See the Full Prescribing Information for:
  - Dosage and administration instructions in adults, pediatric patients, geriatric patients, patients with neuromuscular disease, burns, end-stage renal disease, and patients undergoing coronary artery bypass graft surgery with induced hypothermia (2.2, 2.3, 2.4, 2.5)
  - Continuous infusion rates (2.6)
  - Preparation instructions (2.7)
  - Drug compatibility (2.8)

3 DOSAGE FORMS AND STRENGTHS

Injection:

- 10 mg/5 mL (2 mg/mL) in single-dose vials (3)
- 20 mg/10 mL (2 mg/mL) and benzyl alcohol as a preservative in multiple-dose vials (3)

4 CONTRAINDICATIONS

- Known hypersensitivity to cisatracurium (4)

5 WARNINGS AND PRECAUTIONS

- Residual Paralysis: Patients with neuromuscular diseases are at higher risk. Use a lower initial bolus dose and consider using a reversal agent in these patients. (2.2, 5.1)
- Benzyl Alcohol: Consider combined daily load of benzyl alcohol from all sources when the 10 mL multiple dose vials are used in infants (4, 5.2)
- Risk of Seizure: Monitor level of neuromuscular blockade during long-term administration to limit exposure to toxic metabolites (5.3)
- Hypersensitivity Reactions and Anaphylaxis: Severe hypersensitivity reactions including anaphylactic reactions have been reported. Consider cross-reactivity among neuromuscular blocking agents, both depolarizing and non-depolarizing. (4, 5.4)
- Risk of Death due to Medication Errors: Accidental administration can cause death. (5.5)
- Inadequate Anesthesia: Use cisatracurium besylate in the presence of appropriate sedation or general anesthesia and monitor patients to ensure level of anesthesia is adequate (5.6)

6 ADVERSE REACTIONS

The most common adverse reactions (0.1% to 0.4%) were bradycardia, hypotension, flushing, bronchospasm, and rash. (6.1)
To report SUSPECTED ADVERSE REACTIONS, contact Eugia US LLC at 1-866-850-2876 or FDA at 1-800-FDA-1088 or www.fda.gov/medwatch.

7 DRUG INTERACTIONS

- Succinylcholine: May decrease time to onset of maximum neuromuscular blockade (7.1)
- Inhalational anesthetics, antibiotics, local anesthetics, magnesium salts, procainamide, lithium, quinidine: May potentiate or prolong neuromuscular blockade action of cisatracurium besylate. Use peripheral nerve stimulator and monitor clinical signs of neuromuscular blockade. (5.8, 7.1)
- Phenytoin and Carbamazepine: May shorten duration of neuromuscular blockade. Use peripheral nerve stimulator and monitor clinical signs of neuromuscular blockade. (5.9, 7.1)

8 USE IN SPECIFIC POPULATIONS

- Patients with Hemiparesis or Paraparesis: Perform neuromuscular monitoring on non-paretic limb (8.9)

FULL PRESCRIBING INFORMATION

1 INDICATIONS AND USAGE

Cisatracurium besylate injection is indicated:

- as an adjunct to general anesthesia to facilitate tracheal intubation in adults and in pediatric patients 1 month to 12 years of age
- to provide skeletal muscle relaxation in adults during surgical procedures or during mechanical ventilation in the ICU
- to provide skeletal muscle relaxation during surgical procedures via infusion in pediatric patients 2 years and older

Limitations of Use
Cisatracurium besylate injection is not recommended for rapid sequence endotracheal intubation due to the time required for its onset of action.

2 DOSAGE AND ADMINISTRATION

2.1 Important Dosage and Administration Instructions

Risk of Medication Errors

Accidental administration of neuromuscular blocking agents may be fatal. Store cisatracurium besylate injection with the cap and ferrule intact and in a manner that minimizes the possibility of selecting the wrong product [see Warnings and Precautions (5.5)].

Important Administration Instructions

- Cisatracurium besylate injection is for intravenous use only.
- Administer cisatracurium besylate injection in carefully adjusted dosage by or under the supervision of experienced clinicians who are familiar with the drug’s actions and the possible complications.
- Use cisatracurium besylate injection only if the following are immediately available: personnel and facilities for resuscitation and life support (tracheal intubation, artificial ventilation, oxygen therapy); and an antagonist of cisatracurium besylate injection [see Overdosage (10)].
- The dosage information which follows is intended to serve as an initial guide for individual patients; base subsequent cisatracurium besylate injection dosage on the patients’ responses to the initial doses.
- Use a peripheral nerve stimulator to:
  - Determine the adequacy of neuromuscular blockade (e.g., need for additional cisatracurium besylate injection doses, reduction of the infusion rate).
  - Minimize risk of overdosage or underdosage.
  - Assess the extent of recovery from neuromuscular blockade (e.g., spontaneous recovery or recovery after administration of a reversal agent, e.g., neostigmine).
  - Appropriately titrate doses to potentially limit exposure to toxic metabolites.
  - Facilitate more rapid reversal of the cisatracurium besylate injection-induced paralysis.

2.2 Recommended Cisatracurium Besylate Injection Dose for Performing Tracheal Intubation

Tracheal Intubation in Adults
Prior to selecting the initial cisatracurium besylate injection bolus dose, consider the desired time to tracheal intubation and the anticipated length of surgery, factors affecting time to onset of complete neuromuscular block such as age and renal function, and factors that may influence intubation conditions such as the presence of co-induction agents (e.g., fentanyl and midazolam) and the depth of anesthesia.
In conjunction with a propofol/nitrous oxide/oxygen induction-intubation technique or a thiopental/nitrous oxide/oxygen induction-intubation technique, the recommended starting weight-based dose of cisatracurium besylate injection is between 0.15 mg/kg and 0.2 mg/kg administered by bolus intravenous injection. Doses up to 0.4 mg/kg have been safely administered by bolus intravenous injection to healthy patients and patients with serious cardiovascular disease [see Clinical Pharmacology (12.2)].
Patients with Neuromuscular Disease
The maximum recommended initial bolus dose of cisatracurium besylate injection is 0.02 mg/kg in patients with neuromuscular diseases (e.g., myasthenia gravis and myasthenic syndrome and carcinomatosis) [see Warnings and Precautions (5.1)].
Geriatric Patients and Patients with End-Stage Renal Disease
Because the time to maximum neuromuscular blockade is approximately 1 minute slower in geriatric patients compared to younger patients (and in patients with end-stage renal disease than in patients with normal renal function), consider extending the interval between administering cisatracurium besylate injection and attempting intubation by at least 1 minute to achieve adequate intubation conditions in geriatric patients and patients with end-stage renal disease. A peripheral nerve stimulator should be used to determine the adequacy of muscle relaxation for the purposes of intubation and the timing and amounts of subsequent doses [see Use in Specific Populations (8.5, 8.6) and Clinical Pharmacology (12.3)].
Tracheal Intubation in Pediatric Patients
Infants 1 to 23 Months of Age
The recommended dose of cisatracurium besylate injection for intubation of pediatric patients ages 1 month to 23 months is 0.15 mg/kg administered over 5 to 10 seconds. When administered during stable opioid/nitrous oxide/oxygen anesthesia, 0.15 mg/kg of cisatracurium besylate injection produced maximum neuromuscular blockade in about 2 minutes (range: 1.3 to 4.3 minutes) with a clinically effective block (time to 25% recovery) for about 43 minutes (range: 34 to 58 minutes) [see Clinical Studies (14.2)].
Pediatric Patients 2 to 12 Years of Age
The recommended weight-based bolus dose of cisatracurium besylate injection for pediatric patients 2 to 12 years of age is 0.1 to 0.15 mg/kg administered over 5 to 10 seconds. When administered during stable opioid/nitrous oxide/oxygen anesthesia, 0.1 mg/kg cisatracurium besylate injection produced maximum neuromuscular blockade in an average of 2.8 minutes (range: 1.8 to 6.7 minutes) with a clinically effective block (time to 25% recovery) for 28 minutes (range: 21 to 38 minutes). When administered during stable opioid/nitrous oxide/oxygen anesthesia, 0.15 mg/kg cisatracurium besylate injection produced maximum neuromuscular blockade in an average of about 3 minutes (range: 1.5 to 8 minutes) with a clinically effective block for 36 minutes (range: 29 to 46 minutes) [see Clinical Studies (14.2)].

2.3 Recommended Maintenance Bolus Cisatracurium Besylate Injection Doses in Adult Surgical Procedures

Determine if maintenance bolus doses are needed based on clinical criteria including the response to peripheral nerve stimulation. The recommended maintenance bolus dose of cisatracurium besylate injection is 0.03 mg/kg; however, smaller or larger maintenance doses may be administered based on the required duration of action. Administer the first maintenance bolus dose starting:

- 40 to 50 minutes after an initial dose of cisatracurium besylate injection 0.15 mg/kg;
- 50 to 60 minutes after an initial dose of cisatracurium besylate injection 0.2 mg/kg.

For long surgical procedures using inhalational anesthetics administered with nitrous oxide/oxygen at the 1.25 MAC level for at least 30 minutes, consider administering less frequent maintenance bolus doses or lower maintenance bolus doses of cisatracurium besylate injection [see Clinical Pharmacology (12.2)]. No adjustment to the initial cisatracurium besylate injection maintenance bolus dose should be necessary when cisatracurium besylate injection is administered shortly after initiation of volatile agents or when used in patients receiving propofol anesthesia.

2.4 Dosage in Burn Patients

Burn patients have been shown to develop resistance to nondepolarizing neuromuscular blocking agents; therefore, consider increasing the cisatracurium besylate injection dosages for intubation and maintenance [see Use in Specific Populations (8.8)].

2.5 Dosage for Continuous Infusion

Continuous Infusion for Surgical Procedures in Adults and Pediatric Patients
During extended surgical procedures, cisatracurium besylate injection may be administered by continuous infusion to adults and pediatric patients aged 2 or more years if patients have spontaneous recovery after the initial cisatracurium besylate injection bolus dose. Following recovery from neuromuscular blockade, it may be necessary to re-administer a bolus dose to quickly re-establish neuromuscular blockade prior to starting the continuous infusion.
If patients have had recovery of neuromuscular function, the recommended initial cisatracurium infusion rate is 3 mcg/kg/minute [see Dosage and Administration (2.6)]. Subsequently reduce the rate to 1 to 2 mcg/kg/minute to maintain continuous neuromuscular blockade. Use peripheral nerve stimulation to assess the level of neuromuscular blockade and to appropriately titrate the cisatracurium infusion rate. If no response is elicited to peripheral nerve stimulation, discontinue the infusion until a response returns.
Consider reducing the infusion rate by up to 30% to 40% when cisatracurium besylate injection is administered during stable isoflurane anesthesia for at least 30 minutes (administered with nitrous oxide/oxygen at the 1.25 MAC level) [see Clinical Pharmacology (12.2)]. Greater reductions in the cisatracurium infusion rate may be required with longer durations of administration of isoflurane or with the administration of other inhalational anesthetics.
Patients Undergoing Coronary Artery Bypass Graft (CABG) Surgery
Consider reducing the infusion rate in patients undergoing CABG with induced hypothermia to half the rate required during normothermia [see Clinical Pharmacology (12.2)]. Spontaneous recovery from neuromuscular block following discontinuation of cisatracurium infusion is expected to proceed at a rate comparable to that following administration of a single bolus dose.
Continuous Infusion for Mechanical Ventilation in the Intensive Care Unit in Adults
During extended need for mechanical ventilation and skeletal muscle relaxation in the intensive care unit (ICU), cisatracurium besylate injection may be administered by continuous infusion to adults if a patient has spontaneous recovery of neuromuscular function after the initial cisatracurium besylate injection bolus dose. Following recovery from neuromuscular blockade, it may be necessary to re-administer a bolus dose to quickly re-establish neuromuscular blockade prior to starting the continuous infusion.
The recommended cisatracurium infusion rate in adult patients in the ICU is 3 mcg/kg/minute (range: 0.5 to 10.2 mcg/kg/minute) [see Dosage and Administration (2.6)]. Use peripheral nerve stimulation to assess the level of neuromuscular blockade and to appropriately titrate the cisatracurium infusion rate.

2.6 Rate Tables for Continuous Infusion

The intravenous infusion rate depends upon the cisatracurium besylate injection concentration, the desired dose, the patient's weight, and the contribution of the infusion solution to the fluid requirements of the patient. Tables 1 and 2 provide guidelines for the cisatracurium infusion rate, in mL/hour (equivalent to microdrops/minute when 60 microdrops = 1 mL), in concentrations of 0.1 mg/mL or 0.4 mg/mL, respectively.

Table 1. Cisatracurium Infusion Rates for Maintenance of Neuromuscular Blockade During Opioid/Nitrous Oxide/Oxygen Anesthesia with a Concentration of 0.1 mg/mL
 | Drug Delivery Rate (mcg/kg/minute)
 | 1 | 1.5 | 2 | 3 | 5
Patient Weight | Infusion Delivery Rate (mL/hour)
10 kg | 6 | 9 | 12 | 18 | 30
45 kg | 27 | 41 | 54 | 81 | 135
70 kg | 42 | 63 | 84 | 126 | 210
100 kg | 60 | 90 | 120 | 180 | 300

Table 2. Cisatracurium Infusion Rates for Maintenance of Neuromuscular Blockade During Opioid/Nitrous Oxide/Oxygen Anesthesia with a Concentration of 0.4 mg/mL
 | Drug Delivery Rate (mcg/kg/minute)
 | 1 | 1.5 | 2 | 3 | 5
Patient Weight | Infusion Delivery Rate (mL/hour)
10 kg | 1.5 | 2.3 | 3 | 4.5 | 7.5
45 kg | 6.8 | 10.1 | 13.5 | 20.3 | 33.8
70 kg | 10.5 | 15.8 | 21 | 31.5 | 52.5
100 kg | 15 | 22.5 | 30 | 45 | 75

2.7 Preparation of Cisatracurium Besylate Injection

Visually inspect cisatracurium besylate injection for particulate matter and discoloration prior to administration. If a cisatracurium besylate injection solution is cloudy or contains visible particulates, do not use cisatracurium besylate injection. Cisatracurium besylate injection is a colorless to slightly yellow or greenish-yellow solution.
Discard unused portion of the 5 mL single-dose vials.

Cisatracurium besylate injection may be diluted to 0.1 mg/mL in the following solutions:

- 5% Dextrose Injection, USP
- 0.9% Sodium Chloride Injection, USP, or
- 5% Dextrose and 0.9% Sodium Chloride Injection, USP

Store these diluted cisatracurium besylate injection solutions either in a refrigerator or at room temperature for 24 hours without significant loss of potency.

Cisatracurium besylate injection also may be diluted to 0.1 mg/mL or 0.2 mg/mL in the following solution:

- Lactated Ringer’s and 5% Dextrose Injection

Store this diluted cisatracurium besylate injection solution under refrigeration for no more than 24 hours.

Do not dilute cisatracurium besylate injection in Lactated Ringer’s Injection, USP due to chemical instability.

2.8 Drug Compatibility

Cisatracurium besylate injection is compatible and may be administered with the following solutions through Y-site administration:

- 5% Dextrose Injection, USP
- 0.9% Sodium Chloride Injection, USP
- 5% Dextrose and 0.9% Sodium Chloride Injection, USP
- Sufentanil Citrate Injection, diluted as directed
- Alfentanil Hydrochloride Injection, diluted as directed
- Fentanyl Citrate Injection, diluted as directed
- Midazolam Hydrochloride Injection, diluted as directed
- Droperidol Injection, diluted as directed

Cisatracurium besylate injection is acidic (pH = 3.25 to 3.65) and may not be compatible with alkaline solution having a pH greater than 8.5 (e.g., barbiturate solutions). Therefore, do not administer cisatracurium besylate injection and alkaline solutions simultaneously in the same intravenous line.

Cisatracurium besylate injection is not compatible with propofol injection or ketorolac injection for Y-site administration. Compatibility studies with other parenteral products have not been conducted.

3 DOSAGE FORMS AND STRENGTHS

Cisatracurium besylate injection is available as a clear colorless to slightly yellow or greenish-yellow solution in the following strengths:

- 10 mg of cisatracurium per 5 mL (2 mg/mL) in single-dose vials (equivalent to 2.68 mg/mL cisatracurium besylate)
- 20 mg of cisatracurium per 10 mL (2 mg/mL) in multiple-dose vials (equivalent to 2.68 mg/mL cisatracurium besylate) with benzyl alcohol as a preservative.

4 CONTRAINDICATIONS

- Cisatracurium besylate injection is contraindicated in patients with known hypersensitivity to cisatracurium. Severe anaphylactic reactions to cisatracurium have been reported [see Warnings and Precautions (5.4)].
- The use of 10 mL cisatracurium besylate injection multiple-dose vials is contraindicated for use in pediatric patients less than 1 month of age and low birth-weight infants because the formulation contains benzyl alcohol [see Warnings and Precautions (5.2) and Use in Specific Populations (8.4)].

5 WARNINGS AND PRECAUTIONS

5.1 Residual Paralysis

Cisatracurium has been associated with residual paralysis. Patients with neuromuscular diseases (e.g., myasthenia gravis and myasthenic syndrome) and carcinomatosis may be at higher risk of residual paralysis; thus, a lower maximum initial bolus is recommended in these patients [see Dosage and Administration (2.2) and Use in Specific Populations (8.10)]. To prevent complications resulting from cisatracurium-associated residual paralysis, extubation is recommended only after the patient has recovered sufficiently from neuromuscular blockade. Consider use of a reversal agent especially in cases where residual paralysis is more likely to occur [see Overdosage (10)].

5.2 Risk of Serious Adverse Reactions in Infants due to Benzyl Alcohol Preservative in 10 mL Multiple-Dose Vials

Serious and fatal adverse reactions including “gasping syndrome” can occur in neonates and infants treated with benzyl alcohol-preserved drugs, including cisatracurium (10 mL multiple-dose vials). This warning is not applicable to the 5 mL and 20 mL cisatracurium single-dose vials because these vials do not contain benzyl alcohol. The “gasping syndrome” is characterized by central nervous system depression, metabolic acidosis, and gasping respirations.
When prescribing the 10 mL multiple-dose cisatracurium vials in infants consider the combined daily metabolic load of benzyl alcohol from all sources including cisatracurium (multiple-dose vials contain 9 mg of benzyl alcohol per mL) and other drugs containing benzyl alcohol. The minimum amount of benzyl alcohol at which serious adverse reactions may occur is not known [see Use in Specific Populations (8.4)].
The use of 10 mL cisatracurium multiple-dose vials is contraindicated in pediatric patients less than 1 month of age and low birth-weight infants because these patients are more likely to develop benzyl alcohol toxicity [see Contraindications (4)].

5.3 Risk of Seizure

Laudanosine, an active metabolite of cisatracurium, has been shown to cause seizures in animals. Cisatracurium-treated patients with renal or hepatic impairment may have higher metabolite concentrations (including laudanosine) than patients with normal renal and hepatic function [see Clinical Pharmacology (12.3)]. Therefore, patients with renal or hepatic impairment receiving extended administration of cisatracurium may be at higher risk of seizures.
The level of neuromuscular blockade during long-term cisatracurium administration should be monitored with a nerve stimulator to titrate cisatracurium administration to the patients’ needs and limit exposure to toxic metabolites.

5.4 Hypersensitivity Reactions Including Anaphylaxis

Severe hypersensitivity reactions, including fatal and life-threatening anaphylactic reactions, have been reported [see Contraindications (4)]. There have been reports of wheezing, laryngospasm, bronchospasm, rash and itching following cisatracurium administration in pediatric patients. Due to the potential severity of these reactions, appropriate precautions such as the immediate availability of appropriate emergency treatment should be taken. Precautions should also be taken in those patients who have had previous anaphylactic reactions to other neuromuscular blocking agents since cross-reactivity between neuromuscular blocking agents, both depolarizing and non-depolarizing, has been reported.

5.5 Risk of Death Due to Medication Errors

Administration of cisatracurium results in paralysis, which may lead to respiratory arrest and death, a progression that may be more likely to occur in a patient for whom it is not intended. Confirm proper selection of intended product and avoid confusion with other injectable solutions that are present in critical care and other clinical settings. If another healthcare provider is administering the product, ensure that the intended dose is clearly labeled and communicated.

5.6 Risks Due to Inadequate Anesthesia

Neuromuscular blockade in the conscious patient can lead to distress. Use cisatracurium in the presence of appropriate sedation or general anesthesia. Monitor patients to ensure that the level of anesthesia is adequate.

5.8 Potentiation of Neuromuscular Blockade

Certain drugs may enhance the neuromuscular blocking action of cisatracurium including inhalational anesthetics, antibiotics, magnesium salts, lithium, local anesthetics, procainamide and quinidine [see Drug Interactions (7.1)]. Additionally, acid-base and/or serum electrolyte abnormalities may potentiate the action of neuromuscular blocking agents. Use peripheral nerve stimulation and monitor the clinical signs of neuromuscular blockade to determine the adequacy of the level of neuromuscular blockage and the need to adjust the cisatracurium dosage.

5.9 Resistance to Neuromuscular Blockade with Certain Drugs

Shorter durations of neuromuscular block may occur and cisatracurium infusion rate requirements may be higher in patients chronically administered phenytoin or carbamazepine [see Drug Interactions (7.1) and Clinical Pharmacology (12.3)]. Use peripheral nerve stimulation and monitor the clinical signs of neuromuscular blockade to determine the adequacy of neuromuscular blockage and the need to adjust the cisatracurium dosage.

5.10 Malignant Hyperthermia (MH)

Cisatracurium has not been studied in MH-susceptible patients. Because MH can develop in the absence of established triggering agents, the clinician should be prepared to recognize and treat MH in any patient undergoing general anesthesia.

6 ADVERSE REACTIONS

6.1 Clinical Studies Experience

Because clinical studies are conducted under widely varying conditions, adverse reaction rates observed in the clinical studies of a drug cannot be directly compared to rates in the clinical studies of another drug and may not reflect the rates observed in practice.
Adverse Reactions in Clinical Trials of Cisatracurium in Surgical Patients
The data presented below are based on studies involving 945 surgical patients who received cisatracurium in conjunction with other drugs in US and European clinical studies in a variety of procedures [see Clinical Studies (14.1)].
Table 3 displays adverse reactions that occurred at a rate of less than 1%.

Table 3. Adverse Reactions in Clinical Trials of Cisatracurium in Surgical Patients
Adverse Reaction | Incidence
Bradycardia | 0.4%
Hypotension | 0.2%
Flushing | 0.2%
Bronchospasm | 0.2%
Rash | 0.1%

Adverse Reactions in Clinical Trials of Cisatracurium in Intensive Care Unit Patients
The adverse reactions presented below were from studies involving 68 adult ICU patients who received cisatracurium in conjunction with other drugs in US and European clinical studies [see Clinical Studies (14.3)]. One patient experienced bronchospasm. In one of the two ICU studies, a randomized and double-blind study of ICU patients using TOF neuromuscular monitoring, there were two reports of prolonged recovery (range: 167 and 270 minutes) among 28 patients administered cisatracurium and 13 reports of prolonged recovery (range: 90 minutes to 33 hours) among 30 patients administered vecuronium.

6.2 Postmarketing Experience

The following events have been identified during post-approval use of cisatracurium in conjunction with one or more anesthetic agents in clinical practice. Because they are reported voluntarily from a population of unknown size, estimates of frequency cannot be made. These events have been chosen for inclusion due to a combination of their seriousness, frequency of reporting, or potential causal connection to cisatracurium: anaphylaxis, histamine release, prolonged neuromuscular block, muscle weakness, myopathy.

7 DRUG INTERACTIONS

7.1 Clinically Significant Drug Interactions

Table 4 displays clinically significant drug interactions with cisatracurium.

Table 4. Clinically Significant Drug Interactions with Cisatracurium
Drug or Drug Class | Clinical Implications*
Succinylcholine | The use of succinylcholine prior to cisatracurium administration may decrease the time to onset of maximum neuromuscular blockade but has no effect on the duration of neuromuscular blockade.
Inhalational Anesthetics | Administration of inhalational anesthetics with nitrous oxide/oxygen for greater than 30 minutes to achieve 1.25 Minimum Alveolar Concentration (MAC) may prolong the duration of action of initial and maintenance doses of cisatracurium. This may potentiate the neuromuscular blockade.
Antibiotics† Local anesthetics Magnesium salts Procainamide Lithium Quinidine | May prolong the neuromuscular blockade action of cisatracurium
Phenytoin, Carbamazepine | May increase resistance to the neuromuscular blockade action of cisatracurium resulting in shorter durations of neuromuscular blockade and infusion rate requirements may be higher.
* The use of peripheral nerve stimulator is strongly recommended to evaluate the level of neuromuscular blockade, to assess the need for additional doses of cisatracurium, and to determine whether adjustments need to be made to the dose with subsequent administration.
† Examples: aminoglycosides, tetracyclines, bacitracin, polymyxins, lincomycin, clindamycin, colistin, sodium colistimethate

7.2 Drugs Without Clinically Significant Drug Interactions with Cisatracurium Besylate

In clinical studies, propofol had no effect on the duration of action or dosing requirements for cisatracurium. Cisatracurium is not compatible with propofol for Y-site administration.

8 USE IN SPECIFIC POPULATIONS

8.1 Pregnancy

Risk Summary

The 10 mL cisatracurium besylate injection multiple-dose vials contain the preservative benzyl alcohol. Therefore, if cisatracurium besylate injection is needed during pregnancy, consider using a benzyl alcohol-free formulation (i.e., 5 mL cisatracurium besylate injection single-dose vials). Because benzyl alcohol is rapidly metabolized by a pregnant woman, benzyl alcohol exposure in the fetus is unlikely. However, adverse reactions have occurred in premature neonates and low birth weight infants who received intravenously administered benzyl alcohol-containing drugs [see Contraindications (4), Warnings and Precautions (5.2), and Use in Specific Populations (8.4)].

There are no available clinical trial data on cisatracurium use in pregnancy to evaluate a drug-associated risk of major birth defects, miscarriage, or adverse maternal or fetal outcomes. Animal studies conducted in rats administered cisatracurium besylate during organogenesis (Gestational Day 6 to 15) found no evidence of fetal harm at 0.8 times (ventilated rats) the exposure from a human starting IV bolus dose of 0.2 mg/kg (see Data).

The estimated background risk for major birth defects and miscarriage in the indicated population is unknown. All pregnancies have a background risk of birth defect, loss, or other adverse outcomes. In the U.S. general population, the estimated background risk of major birth defects and miscarriage in clinically recognized pregnancies is 2 to 4% and 15 to 20%, respectively.

Clinical Considerations

Labor or Delivery

The action of neuromuscular blocking agents may be enhanced by magnesium salts administered for the management of preeclampsia or eclampsia of pregnancy.

Data

Animal Data

Two embryofetal developmental reproductive toxicity studies were conducted in rats. In a non- ventilated rat study, pregnant animals were treated with cisatracurium besylate subcutaneously twice per day from Gestational Day 6 to 15 using subparalyzing doses (2 and 4 mg/kg daily; equivalent to 6- and 12-times, respectively, the AUC exposure in humans following a bolus dose of 0.2 mg/kg IV). In the ventilated rat study, pregnant animals were treated with cisatracurium besylate intravenously once a day between Gestational Day 6 to 15 using paralyzing doses (0.5 and 1 mg/kg; equivalent to 0.4- and 0.8-times, respectively, the exposure in humans following a bolus dose of 0.2 mg/kg IV based on mg/m^2 comparison). Neither of these studies revealed maternal or fetal toxicity or malformations.

8.2 Lactation

Risk Summary

The 10 mL cisatracurium besylate injection multiple-dose vials contains the preservative benzyl alcohol. Therefore, if cisatracurium besylate injection is needed during lactation, consider using a benzyl alcohol-free formulation (i.e., 5 mL cisatracurium besylate injection single-dose vials). Because benzyl alcohol is rapidly metabolized by a lactating woman, benzyl alcohol exposure in the breastfed infant is unlikely. However, adverse reactions have occurred in premature neonates and low birth weight infants who received intravenously administered benzyl alcohol-containing drugs [see Contraindications (4), Warnings and Precautions (5.2) and Use in Specific Populations (8.4)].

There are no data on the presence of cisatracurium besylate in human milk, the effects on the breastfed child, or the effects on milk production. The developmental and health benefits of breastfeeding should be considered along with the mother's clinical need for cisatracurium and any potential adverse effects on the breastfed child from cisatracurium or from the underlying maternal condition.

8.4 Pediatric Use

The safety and effectiveness of cisatracurium as an adjunct to general anesthesia to facilitate tracheal intubation, and to provide skeletal muscle relaxation during surgery in pediatric patients 1 month through 12 years of age were established from three studies in pediatric patients [see Dosing and Administration (2.2, 2.5) and Clinical Studies (14.2)]. The three open-label studies are summarized below.
The safety and effectiveness of cisatracurium have not been established in pediatric patients less than 1 month of age.
Tracheal Intubation
A study of 0.15 mg/kg cisatracurium evaluated 230 pediatric patients (ages 1 month to 12 years). Excellent or good intubating conditions were produced 120 seconds following 0.15 mg/kg of cisatracurium in 88 of 90 of patients induced with halothane and in 85 of 90 of patients induced with thiopentone and fentanyl. The study also evaluated 50 pediatric patients during opioid anesthesia, with maximum neuromuscular blockade achieved in an average of about 3 minutes and a clinically effective block for 36 minutes in patients ages 2 to 12 years, and maximum neuromuscular block in about 2 minutes and a clinically effective block for about 43 minutes in infants 1 to 23 months [see Clinical Studies (14.2)].
In a study of 0.1 mg/kg cisatracurium administered in 16 pediatric patients (ages 2 to 12 years) during opioid/nitrous oxide/oxygen anesthesia, maximum neuromuscular blockade was achieved in an average of 2.8 minutes with a clinically effective block for 28 minutes [see Clinical Studies (14.2)].
Skeletal Muscle Relaxation During Surgery
In a study of cisatracurium administered during halothane/nitrous oxide/oxygen anesthesia, 18 pediatric patients (ages 2 to 12 years) were scheduled for surgical procedures that required neuromuscular block for 60 minutes or longer. The average duration of continuous infusion was 62.8 minutes (range: 17 to 145 minutes). The overall mean infusion rate for 9 patients whose infusion was 45 minutes or longer was 1.7 mcg/kg/minute (range: 1.19 to 2.14 mcg/kg/minute).
Serious Adverse Reactions in InfantsDue to BenzylAlcoholPreservative in 10 mLMultiple-Dose Vials
Seriousadversereactionsincludingfatalreactionsand the “gasping syndrome” occurred in premature neonatesandinfants in the neonatal intensive care unit whoreceiveddrugs containing benzylalcoholas a preservative.Inthesecases,benzylalcoholdosages of 99 to 234 mg/kg/dayproducedhighlevels of benzylalcoholand its metabolites in the blood andurine (bloodlevels of benzylalcoholwere 0.61 to 1.378 mmol/L).Additionaladversereactionsincludedgradualneurologicaldeterioration,seizures,intracranialhemorrhage,hematologicabnormalities, skin breakdown, hepatic andrenalfailure,hypotension,bradycardia,andcardiovascularcollapse. Preterm,low-birthweightinfants may be more likely to develop these reactions because they may be lessable to metabolize benzyl alcohol.
When prescribing the 10 mLmultiple-dose cisatracurium vials in infantsconsider the combined daily metabolic loadof benzylalcohol from allsources including cisatracurium (multiple-dose vialscontain 9 mg of benzyl alcohol per mL) and other drugscontainingbenzylalcohol.The minimum amount of benzylalcoholatwhich serious adversereactionsmay occur is not known[seeWarnings and Precautions (5.2)]. This warning is not applicable to the 5 mL and 20 mL cisatracurium single-dose vials because these vials do not contain benzyl alcohol.
The use of 10 mL cisatracurium multiple-dose vials is contraindicated in pediatric patients less than 1 month of age and low birth-weight infants because these patients are more likely to develop benzyl alcohol toxicity.

8.5 Geriatric Use

Of the total number of subjects (135) in clinical studies of cisatracurium, 57, 63, and 15 subjects were 65 to 70 years old, 70 to 80 years old, and greater than 80 years old, respectively. The geriatric population included a subset of patients with significant cardiovascular disease [see Clinical Pharmacology (12.3)].
Because the time to maximum neuromuscular blockade is approximately 1 minute slower in geriatric patients compared to younger patients, consider extending the interval between administering cisatracurium and attempting intubation by at least 1 minute to achieve adequate intubation conditions [see Dosage and Administration (2.2) and Clinical Pharmacology (12.2)].
The time to maximum neuromuscular blockade is approximately 1 minute slower in geriatric patients, a difference that should be taken into account when selecting a neuromuscular blocking agent (e.g., the need to rapidly secure the airway) and when initiating laryngoscopy [see Clinical Pharmacology (12.3)]. Minor differences in the pharmacokinetics of cisatracurium between elderly and young adult patients were not associated with clinically significant differences in the recovery profile of cisatracurium following a single 0.1 mg/kg dose.
Besides the differences noted above, no overall differences in safety or effectiveness were observed between geriatric and younger subjects, and other reported clinical experience has not identified differences in responses between geriatric and younger subjects, but greater sensitivity of some older individuals to cisatracurium cannot be ruled out.

8.6 Patients with Renal Impairment

The time to 90% neuromuscular blockade was 1 minute slower in patients with end-stage renal disease than in patients with normal renal function. Therefore, consider extending the interval between administering cisatracurium and attempting intubation by at least 1 minute to achieve adequate intubation conditions [see Dosage and Administration (2.2) and Clinical Pharmacology (12.2)].
There was no clinically significant alteration in the recovery profile of cisatracurium in patients with end-stage renal disease following a 0.1 mg/kg dose of cisatracurium. The recovery profile of cisatracurium is unchanged in patients with renal impairment, which is consistent with predominantly organ-independent elimination [see Clinical Pharmacology (12.3)].

8.7 Patients with Hepatic Impairment

The pharmacokinetic study analysis in patients with end-stage liver disease undergoing liver transplantation and healthy subjects undergoing elective surgery indicated slightly larger volumes of distribution in liver transplant patients with slightly higher plasma clearances of cisatracurium. The times to maximum neuromuscular blockade were approximately one minute faster in liver transplant patients than in healthy adult patients receiving 0.1 mg/kg cisatracurium. These minor differences in pharmacokinetics were not associated with clinically significant differences in the recovery profile of cisatracurium [see Clinical Pharmacology (12.3)].

8.8 Burn Patients

Patients with burns have been shown to develop resistance to nondepolarizing neuromuscular blocking agents. The extent of altered response depends upon the size of the burn and the time elapsed since the burn injury. Cisatracurium has not been studied in patients with burns. However, based on its structural similarity to another neuromuscular blocking agent, consider the possibility of increased dosage requirements and shortened duration of action if cisatracurium is administered to burn patients.

8.9 Patients with Hemiparesis or Paraparesis

Patients with hemiparesis or paraparesis may demonstrate resistance to nondepolarizing neuromuscular blocking agents in the affected limbs. To avoid inaccurate dosing, perform neuromuscular monitoring on a non-paretic limb.

8.10 Patients with Neuromuscular Disease

Profound and prolonged neuromuscular blockade may occur in patients with neuromuscular diseases (e.g., myasthenia gravis and myasthenic syndrome) and carcinomatosis. Therefore, a lower maximum initial bolus is recommended in these patients [see Dosage and Administration (2.2)].

10 OVERDOSAGE

Overdosage with neuromuscular blocking agents may result in neuromuscular blockade beyond the time needed for surgery and anesthesia. The primary treatment is maintenance of a patent airway and controlled ventilation until recovery of normal neuromuscular function is assured.
Once recovery from neuromuscular block begins, further recovery may be facilitated by administration of a cholinesterase inhibitor (e.g., neostigmine, edrophonium) in conjunction with an appropriate cholinergic inhibitor. Cholinesterase inhibitors should not be administered when complete neuromuscular blockade is evident or suspected because the reversal of paralysis may not be sufficient to maintain a patent airway and support an appropriate level of spontaneous ventilation.

- Neostigmine: Administration of 0.04 to 0.07 mg/kg of neostigmine at approximately 10% recovery from neuromuscular blockade (range: 0 to 15%) produced 95% recovery of the muscle twitch response and a T4:T1 ratio ≥ 70% in an average of 9 to 10 minutes. The times from 25% recovery of the muscle twitch response to a T4:T1 ratio ≥ 70% following these doses of neostigmine averaged 7 minutes. The mean 25% to 75% recovery index following reversal was 3 to 4 minutes.
- Edrophonium: Administration of 1 mg/kg of edrophonium at approximately 25% recovery from neuromuscular blockade (range: 16% to 30%) produced 95% recovery and a T4:T1 ratio ≥ 70% in an average of 3 to 5 minutes.

For providers treating patients treated with cholinesterase inhibitors:

- Use a peripheral nerve stimulator to evaluate recovery and antagonism of neuromuscular blockade.
- Evaluate for evidence of adequate clinical recovery (e.g., 5-second head lift and grip strength).
- Support ventilation until adequate spontaneous ventilation has resumed.

The onset of antagonism may be delayed in the presence of debilitation, cachexia, carcinomatosis, and the concomitant use of certain broad spectrum antibiotics, or anesthetic agents and other drugs which enhance neuromuscular block or separately cause respiratory depression [see Drug Interactions (7.1)]. Under such circumstances the management is the same as that of prolonged neuromuscular block.

11 DESCRIPTION

Cisatracurium besylate injection, USP is a nondepolarizing skeletal neuromuscular blocker for intravenous administration. Compared to other neuromuscular blockers, it is intermediate in its onset and duration of action. Cisatracurium besylate injection, USP contains cisatracurium besylate as the active pharmaceutical ingredient.
Cisatracurium besylate is one of 10 isomers of atracurium besylate and constitutes approximately 15% of that mixture. Cisatracurium besylate is [1R-[1α,2α(1'R*,2'R*)]]-2,2'-[1,5-pentanediylbis[oxy(3-oxo-3,1-propanediyl)]]bis[1-[(3,4-dimethoxyphenyl)methyl]-1,2,3,4-tetrahydro-6,7-dimethoxy-2-methylisoquinolinium] dibenzenesulfonate. The molecular formula of the cisatracurium parent bis-cation is C53H72N2O12 and the molecular weight is 929.2. The molecular formula of cisatracurium as the besylate salt is C65H82N2O18S2 and the molecular weight is 1243.49. The structural formula of cisatracurium besylate is:

The log of the partition coefficient of cisatracurium besylate is -2.12 in a 1-octanol/distilled water system at 25°C.

Cisatracurium besylate injection, USP is a sterile, non-pyrogenic, clear colorless to slightly yellow or greenish-yellow solution.

Each mL in the single-dose vials contains 2 mg of cisatracurium (equivalent to 2.68 mg of cisatracurium besylate, USP), and benzenesulfonic acid as pH adjuster in water for injection.

Each mL in the multiple-dose vials contains 2 mg of cisatracurium (equivalent to 2.68 mg of cisatracurium besylate, USP), benzenesulfonic acid as pH adjuster, and also contains 9 mg of benzyl alcohol as preservative, in water for injection.

The pH of cisatracurium besylate injection, USP is between 3.0 and 3.8.

12 CLINICAL PHARMACOLOGY

12.1 Mechanism of Action

Cisatracurium binds competitively to cholinergic receptors on the motor end-plate to antagonize the action of acetylcholine, resulting in blockade of neuromuscular transmission. This action is antagonized by acetylcholinesterase inhibitors such as neostigmine.

12.2 Pharmacodynamics

The average ED95 (dose required to produce 95% suppression of the adductor pollicis muscle twitch response to ulnar nerve stimulation) of cisatracurium is 0.05 mg/kg (range: 0.048 to 0.053) in adults receiving opioid/nitrous oxide/oxygen anesthesia.
The pharmacodynamics of various cisatracurium doses administered over 5 to 10 seconds during opioid/nitrous oxide/oxygen anesthesia are summarized in Table 5. When the cisatracurium dose is doubled, the clinically effective duration of blockade increases by approximately 25 minutes. Once recovery begins, the rate of recovery is independent of dose.
Isoflurane or enflurane administered with nitrous oxide/oxygen to achieve 1.25 MAC (Minimum Alveolar Concentration) prolonged the clinically effective duration of action of initial and maintenance cisatracurium doses, and decreased the average infusion rate requirement of cisatracurium. The magnitude of these effects depended on the duration of administration of the volatile agents:

- Fifteen to 30 minutes of exposure to 1.25 MAC isoflurane or enflurane had minimal effects on the duration of action of initial doses of cisatracurium.
- In surgical procedures during enflurane or isoflurane anesthesia greater than 30 minutes, less frequent maintenance dosing, lower maintenance doses, or reduced infusion rates of cisatracurium were required. The average infusion rate requirement was decreased by as much as 30% to 40% [see Drug Interactions (7.1)].

The onset, duration of action, and recovery profiles of cisatracurium during propofol/oxygen or propofol/nitrous oxide/oxygen anesthesia were similar to those during opioid/nitrous oxide/oxygen anesthesia (see Table 5).
Repeated administration of maintenance cisatracurium doses or a continuous cisatracurium infusion for up to 3 hours was not associated with development of tachyphylaxis or cumulative neuromuscular blocking effects. The time needed to recover from successive maintenance doses did not change with the number of doses administered when partial recovery occurred between doses. The rate of spontaneous recovery of neuromuscular function after cisatracurium infusion was independent of the duration of infusion and comparable to the rate of recovery following initial doses (see Table 5).
Pediatric patients including infants generally had a shorter time to maximum neuromuscular blockade and a faster recovery from neuromuscular blockade compared to adults treated with the same weight-based doses (see Table 5).

Table 5. Pharmacodynamic Dose Response* of Cisatracurium During Opioid/Nitrous Oxide/Oxygen Anesthesia
Cisatracurium Dose | Time to 90% Block in minutes | Time to Maximum Block in minutes | 5% Recovery in minutes | 25% Recovery† in minutes | 95% Recovery in minutes | T4:T1 Ratio‡≥ 70% in minutes | 25% to 75% Recovery Index in minutes
Adults
0.1 mg/kg (2 × ED95) (n§ = 98) | 3.3 (1.0 to 8.7) | 5.0 (1.2 to 17.2) | 33 (15 to 51) | 42 (22 to 63) | 64 (25 to 93) | 64 (32 to 91) | 13 (5 to 30)
0.15|| mg/kg (3 × ED95) (n = 39) | 2.6 (1.0 to 4.4) | 3.5 (1.6 to 6.8) | 46 (28 to 65) | 55 (44 to 74) | 76 (60 to 103) | 75 (63 to 98) | 13 (11 to 16)
0.2 mg/kg (4 × ED95) (n = 30) | 2.4 (1.5 to 4.5) | 2.9 (1.9 to 5.2) | 59 (31 to 103) | 65 (43 to 103) | 81 (53 to 114) | 85 (55 to 114) | 12 (2 to 30)
0.25 mg/kg (5 × ED95) (n = 15) | 1.6 (0.8 to 3.3) | 2.0 (1.2 to 3.7) | 70 (58 to 85) | 78 (66 to 86) | 91 (76 to 109) | 97 (82 to 113) | 8 (5 to 12)
0.4 mg/kg (8 × ED95) (n = 15) | 1.5 (1.3 to 1.8) | 1.9 (1.4 to 2.3) | 83 (37 to 103) | 91 (59 to 107) | 121 (110 to 134) | 126 (115 to 137) | 14 (10 to 18)
Infants (1 to 23 months of age)
0.15 mg/kg** (n = 18 to 26) | 1.5 (0.7 to 3.2) | 2.0 (1.3 to 4.3) | 36 (28 to 50) | 43 (34 to 58) | 64 (54 to 84) | 59 (49 to 76) | 11.3 (7.3 to 18.3)
Pediatric Patients 2 to 12 years
0.08 mg/kg¶ (2 × ED95) (n = 60) | 2.2 (1.2 to 6.8) | 3.3 (1.7 to 9.7) | 22 (11 to 38) | 29 (20 to 46) | 52 (37 to 64) | 50 (37 to 62) | 11 (7 to 15)
0.1 mg/kg (n = 16) | 1.7 (1.3 to 2.7) | 2.8 (1.8 to 6.7) | 21 (13 to 31) | 28 (21 to 38) | 46 (37 to 58) | 44 (36 to 58) | 10 (7 to 12)
0.15 mg/kg** (n = 23 to 24) | 2.1 (1.3 to 2.8) | 3.0 (1.5 to 8.0) | 29 (19 to 38) | 36 (29 to 46) | 55 (45 to 72) | 54 (44 to 66) | 10.6 (8.5 to 17.7)
* Values shown are the median values from the means from individual studies. Values in parentheses are ranges of individual patient values.
† Clinically effective duration of block
‡ Train-of-four ratio
§ n = the number of patients with Time to Maximum Block data
|| Propofol anesthesia
¶ Halothane anesthesia
**Thiopentone, alfentanil, N2O/O2 anesthesia

Hemodynamics Profile
Cisatracurium had no dose-related effects on mean arterial blood pressure (MAP) or heart rate (HR) following doses ranging from 0.1 mg/kg to 0.4 mg/kg, administered over 5 to 10 seconds, in healthy adult patients (see Figure 1) or in patients with serious cardiovascular disease (see Figure 2).
A total of 141 patients undergoing coronary artery bypass graft (CABG) surgery were administered cisatracurium in three active-controlled clinical trials and received doses ranging from 0.1 mg/kg to 0.4 mg/kg. While the hemodynamic profile was comparable in both the cisatracurium and active control groups, data for doses above 0.3 mg/kg in this population are limited.
Figure 1. Maximum Percent Change from Preinjection in HR and MAP During First 5 Minutes after Initial 4 × ED95 to 8 × ED95 Cisatracurium Doses in
Healthy Adults Who Received Opioid/Nitrous Oxide/Oxygen Anesthesia (n = 44)

Figure 2. Percent Change from Preinjection in HR and MAP 10 Minutes After an Initial 4 × ED95 to 8 × ED95 Cisatracurium Dose in Patients
Undergoing CABG Surgery Receiving Oxygen/Fentanyl/Midazolam/Anesthesia (n = 54)
No clinically significant changes in MAP or HR were observed following administration of doses up to 0.1 mg/kg cisatracurium over 5 to 10 seconds in 2- to 12-year-old pediatric patients who received either halothane/nitrous oxide/oxygen or opioid/nitrous oxide/oxygen anesthesia. Doses of 0.15 mg/kg cisatracurium administered over 5 seconds were not consistently associated with changes in HR and MAP in pediatric patients aged 1 month to 12 years who received opioid/nitrous oxide/oxygen or halothane/nitrous oxide/oxygen anesthesia.

12.3 Pharmacokinetics

The neuromuscular blocking activity of cisatracurium is due to parent drug. Cisatracurium plasma concentration-time data following IV bolus administration are best described by a two-compartment open model (with elimination from both compartments) with an elimination half-life (t½β) of 22 minutes, a plasma clearance (CL) of 4.57 mL/min/kg, and a volume of distribution at steady state (VSS) of 145 mL/kg.
Results from population pharmacokinetic/pharmacodynamic (PK/PD) analyses from 241 healthy surgical patients are summarized in Table 6.

Table 6. Key Population PK/PD Parameter Estimates for Cisatracurium in Healthy Surgical Patients* Following 0.1 (2 × ED95) to 0.4 mg/kg (8 × ED95) of Cisatracurium
Parameter | Estimate† | Magnitude of Interpatient Variability (CV)‡
CL (mL/min/kg) | 4.57 | 16%
VSS (mL/kg)§ | 145 | 27%
keo (min-1)|| | 0.0575 | 61%
EC50 (ng/mL)¶ | 141 | 52%
* Healthy male non-obese patients 19 to 64 years of age with creatinine clearance values greater than 70 mL/minute who received cisatracurium during opioid anesthesia and had venous samples collected
† The percent standard error of the mean (%SEM) ranged from 3% to 12% indicating good precision for the PK/PD estimates.
‡ Expressed as a coefficient of variation; the %SEM ranged from 20% to 35% indicating adequate precision for the estimates of interpatient variability.
§ Vss is the volume of distribution at steady state estimated using a two-compartment model with elimination from both compartments. Vss is equal to the sum of the volume in the central compartment (Vc) and the volume in the peripheral compartment (Vp); interpatient variability could only be estimated for Vc.
|| Rate constant describing the equilibration between plasma concentrations and neuromuscular block
¶ Concentration required to produce 50% T1 suppression; an index of patient sensitivity.

The magnitude of interpatient variability in CL was low (16%), as expected based on the importance of Hofmann elimination. The magnitudes of interpatient variability in CL and volume of distribution were low in comparison to those for keoand EC50. This suggests that any alterations in the time course of cisatracurium-induced neuromuscular blockade were more likely to be due to variability in the PD parameters than in the PK parameters. Parameter estimates from the population PK analyses were supported by noncompartmental PK analyses on data from healthy patients and from specific populations.
Conventional PK analyses have shown that the PK of cisatracurium are proportional to dose between 0.1 (2 × ED95) and 0.2 (4 × ED95) mg/kg cisatracurium. In addition, population PK analyses revealed no statistically significant effect of initial dose on CL for doses between 0.1 (2 × ED95) and 0.4 (8 × ED95) mg/kg cisatracurium.
Distribution
The volume of distribution of cisatracurium is limited by its large molecular weight and high polarity. The Vss was equal to 145 mL/kg (Table 6) in healthy 19- to 64-year-old surgical patients receiving opioid anesthesia. The Vss was 21% larger in similar patients receiving inhalation anesthesia.
The binding of cisatracurium to plasma proteins has not been successfully studied due to its rapid degradation at physiologic pH. Inhibition of degradation requires nonphysiological conditions of temperature and pH which are associated with changes in protein binding.
Elimination
Organ-independent Hofmann elimination (a chemical process dependent on pH and temperature) is the predominant pathway for the elimination of cisatracurium. The liver and kidney play a minor role in the elimination of cisatracurium but are primary pathways for the elimination of metabolites. Therefore, the t½β values of metabolites (including laudanosine) are longer in patients with renal or hepatic impairment and metabolite concentrations may be higher after long-term administration [see Warnings and Precautions (5.3)].
The mean CL values for cisatracurium ranged from 4.5 to 5.7 mL/min/kg in studies of healthy surgical patients. The compartmental PK modeling suggests that approximately 80% of the cisatracurium CL is accounted for by Hofmann elimination and the remaining 20% by renal and hepatic elimination. These findings are consistent with the low magnitude of interpatient variability in CL (16%) estimated as part of the population PK/PD analyses and with the recovery of parent and metabolites in urine.
In studies of healthy surgical patients, mean t½β values of cisatracurium ranged from 22 to 29 minutes and were consistent with the t½β of cisatracurium in vitro (29 minutes). The mean ± SD t½β values of laudanosine were 3.1 ± 0.4 hours in healthy surgical patients receiving cisatracurium (n = 10).
Metabolism:
The degradation of cisatracurium was largely independent of liver metabolism. Results from in vitro experiments suggest that cisatracurium undergoes Hofmann elimination (a pH and temperature-dependent chemical process) to form laudanosine [see Warnings and Precautions (5.3)] and the monoquaternary acrylate metabolite, neither of which has any neuromuscular blocking activity. The monoquaternary acrylate undergoes hydrolysis by non-specific plasma esterases to form the monoquaternary alcohol (MQA) metabolite. The MQA metabolite can also undergo Hofmann elimination but at a much slower rate than cisatracurium. Laudanosine is further metabolized to desmethyl metabolites which are conjugated with glucuronic acid and excreted in the urine.
The laudanosine metabolite of cisatracurium has been noted to cause transient hypotension and, in higher doses, cerebral excitatory effects when administered to several animal species. The relationship between CNS excitation and laudanosine concentrations in humans has not been established [see Warnings and Precautions (5.3)].
During IV infusions of cisatracurium, peak plasma concentrations (Cmax) of laudanosine and the MQA metabolite were approximately 6% and 11% of the parent compound, respectively. The Cmaxvalues of laudanosine in healthy surgical patients receiving infusions of cisatracurium were mean ± SD Cmax: 60 ± 52 ng/mL.
Excretion:
Following ^14C-cisatracurium administration to 6 healthy male patients, 95% of the dose was recovered in the urine (mostly as conjugated metabolites) and 4% in the feces; less than 10% of the dose was excreted as unchanged parent drug in the urine. In 12 healthy surgical patients receiving non-radiolabeled cisatracurium who had Foley catheters placed for surgical management, approximately 15% of the dose was excreted unchanged in the urine.
Special Populations
Geriatric Patients
The results of conventional PK analysis from a study of 12 healthy elderly patients and 12 healthy young adult patients who received a single IV cisatracurium dose of 0.1 mg/kg are summarized in Table 7. Plasma clearances of cisatracurium were not affected by age; however, the volumes of distribution were slightly larger in elderly patients than in young patients resulting in slightly longer t½β values for cisatracurium.
The rate of equilibration between plasma cisatracurium concentrations and neuromuscular blockade was slower in elderly patients than in young patients (mean ± SD keo: 0.071 ± 0.036 and 0.105 ± 0.021 minutes^-1, respectively); there was no difference in the patient sensitivity to cisatracurium-induced block, as indicated by EC50values (mean ± SD EC50: 91 ± 22 and 89 ± 23 ng/mL, respectively). These changes were consistent with the 1-minute slower times to maximum block in elderly patients receiving 0.1 mg/kg cisatracurium, when compared to young patients receiving the same dose. The minor differences in PK/PD parameters of cisatracurium between elderly patients and young patients were not associated with clinically significant differences in the recovery profile of cisatracurium.

Table 7. Pharmacokinetic Parameters* of Cisatracurium in Healthy Elderly and Young Adult Patients Following 0.1 mg/kg (2 × ED95) of Cisatracurium (Isoflurane/Nitrous Oxide/Oxygen Anesthesia)
Parameter | Healthy Elderly Patients | Healthy Young Adult Patients
Elimination Half-Life (t½β, min) | 25.8 ± 3.6† | 22.1 ± 2.5
Volume of Distribution at Steady State‡ (mL/kg) | 156 ± 17† | 133 ± 15
Plasma Clearance (mL/min/kg) | 5.7 ± 1.0 | 5.3 ± 0.9
* Values presented are mean ± SD.
† P < 0.05 for comparisons between healthy elderly and healthy young adult patients
‡ Volume of distribution is underestimated because elimination from the peripheral compartment is ignored.

Patients with Hepatic Impairment:
Table 8 summarizes the conventional PK analysis from a study of cisatracurium in 13 patients with end-stage liver disease undergoing liver transplantation and 11 healthy adult patients undergoing elective surgery. The slightly larger volumes of distribution in liver transplant patients were associated with slightly higher plasma clearances of cisatracurium. The parallel changes in these parameters resulted in no difference in t½β values. There were no differences in keo or EC50 between patient groups. The times to maximum neuromuscular blockade were approximately one minute faster in liver transplant patients than in healthy adult patients receiving 0.1 mg/kg cisatracurium. These minor PK differences were not associated with clinically significant differences in the recovery profile of cisatracurium.

The t½β values of metabolites are longer in patients with hepatic disease and concentrations may be higher after long-term administration.

Table 8. Pharmacokinetic Parameters* of Cisatracurium in Healthy Adult Patients and in Patients Undergoing Liver Transplantation Following 0.1 mg/kg (2 × ED95) of Cisatracurium (Isoflurane/Nitrous Oxide/Oxygen Anesthesia)
Parameter | Liver Transplant Patients | Healthy Adult Patients
Elimination Half-Life (t½β, min) | 24.4 ± 2.9 | 23.5 ± 3.5
Volume of Distribution at Steady State‡(mL/kg) | 195 ± 38† | 161 ± 23
Plasma Clearance (mL/min/kg) | 6.6 ± 1.1† | 5.7 ± 0.8
* Values presented are mean ± SD.
† P < 0.05 for comparisons between liver transplant patients and healthy adult patients
‡ Volume of distribution is underestimated because elimination from the peripheral compartment is ignored.

Patients with Renal Impairment: Results from a conventional PK study of cisatracurium in 13 healthy adult patients and 15 patients with end-stage renal disease (ESRD) who had elective surgery are summarized in Table 9. The PK/PD parameters of cisatracurium were similar in healthy adult patients and ESRD patients. The times to 90% neuromuscular blockade were approximately one minute slower in ESRD patients following 0.1 mg/kg cisatracurium. There were no differences in the durations or rates of recovery of cisatracurium between ESRD and healthy adult patients.

The t½β values of metabolites are longer in patients with ESRD and concentrations may be higher after long-term administration.

Population PK analyses showed that patients with creatinine clearances ≤ 70 mL/min had a slower rate of equilibration between plasma concentrations and neuromuscular block than patients with normal renal function; this change was associated with a slightly slower (~ 40 seconds) predicted time to 90% T1 suppression in patients with renal impairment following 0.1 mg/kg cisatracurium. There was no clinically significant alteration in the recovery profile of cisatracurium in patients with renal impairment. The recovery profile of cisatracurium is unchanged in the presence of renal or hepatic failure, which is consistent with predominantly organ-independent elimination.

Table 9. Pharmacokinetic Parameters* for Cisatracurium in Healthy Adult Patients and in Patients with End-Stage Renal Disease (ESRD) Who Received 0.1 mg/kg (2 × ED95) of Cisatracurium (Opioid/Nitrous Oxide/Oxygen Anesthesia)
Parameter | Healthy Adult Patients | ESRD Patients
Elimination Half-Life (t½β, min) | 29.4 ± 4.1 | 32.3 ± 6.3
Volume of Distribution at Steady State† (mL/kg) | 149 ± 35 | 160 ± 32
Plasma Clearance (mL/min/kg) | 4.66 ± 0.86 | 4.26 ± 0.62
* Values presented are mean ± SD.
† Volume of distribution is underestimated because elimination from the peripheral compartment is ignored.

Intensive Care Unit (ICU) Patients:

The PK of cisatracurium and its metabolites were determined in six ICU patients who received cisatracurium and are presented in Table 10. The relationships between plasma cisatracurium concentrations and neuromuscular blockade have not been evaluated in ICU patients.

Limited PK data are available for ICU patients with hepatic or renal impairment who received cisatracurium. Relative to cisatracurium-treated ICU patients with normal renal and hepatic function, metabolite concentrations (plasma and tissues) may be higher in cisatracurium-treated ICU patients with renal or hepatic impairment [see Warnings and Precautions (5.3)].

Table 10. Parameter Estimates* for Cisatracurium and Metabolites in ICU Patients After Long-Term (24 to 48 Hour) Administration of Cisatracurium
 | Parameter | Cisatracurium (n = 6)
Parent Compound | CL (mL/min/kg) | 7.45 ± 1.02
Parent Compound | t½ β (min) | 26.8 ± 11.1
Parent Compound | Vβ (mL/kg)† | 280 ± 103
Laudanosine | Cmax (ng/mL) | 707 ± 360
Laudanosine | t½β (hrs) | 6.6 ± 4.1
MQA metabolite | Cmax (ng/mL) | 152 to 181‡
MQA metabolite | t½β (min) | 26 to 31‡
* Presented as mean ± standard deviation
† Volume of distribution during the terminal elimination phase, an underestimate because elimination from the peripheral compartment is ignored.
‡ n = 2, range presented

Pediatric Population: The population PK/PD of cisatracurium were described in 20 healthy pediatric patients ages 2 to 12 years during halothane anesthesia, using the same model developed for healthy adult patients. The CL was higher in healthy pediatric patients (5.89 mL/min/kg) than in healthy adult patients (4.57 mL/min/kg) during opioid anesthesia. The rate of equilibration between plasma concentrations and neuromuscular blockade, as indicated by keo, was faster in healthy pediatric patients receiving halothane anesthesia (0.1330 minutes^-1) than in healthy adult patients receiving opioid anesthesia (0.0575 minutes^-1). The EC50 in healthy pediatric patients (125 ng/mL) was similar to the value in healthy adult patients (141 ng/mL) during opioid anesthesia. The minor differences in the PK/PD parameters of cisatracurium were associated with a faster time to onset and a shorter duration of cisatracurium-induced neuromuscular blockade in pediatric patients.

Sex and Obesity:

Although population PK/PD analyses revealed that sex and obesity were associated with effects on the PK and/or PD of cisatracurium; these PK/PD changes were not associated with clinically significant alterations in the predicted onset or recovery profile of cisatracurium.

Use of Inhalation Agents:

The use of inhalation agents was associated with a 21% larger Vss, a 78% larger keo, and a 15% lower EC50 for cisatracurium. These changes resulted in a slightly faster (~ 45 seconds) predicted time to 90% T1suppression in patients who received 0.1 mg/kg cisatracurium during inhalation anesthesia than in patients who received the same dose of cisatracurium during opioid anesthesia; however, there were no clinically significant differences in the predicted recovery profile of cisatracurium between patient groups.

Drug Interaction Studies

Carbamazepine and phenytoin:

The systemic clearance of cisatracurium was higher in patients who were on prior chronic anticonvulsant therapy of carbamazepine or phenytoin [see Warning and Precautions (5.9) and Drug Interactions (7.1)].

13 NONCLINICAL TOXICOLOGY

13.1 Carcinogenesis, Mutagenesis, Impairment of Fertility

Carcinogenesis
Long-term animal studies to evaluate the carcinogenic potential of cisatracurium besylate have not been performed.
Mutagenesis
Cisatracurium besylate was evaluated in a battery of four genotoxicity assays. Evaluation of cisatracurium besylate in the in vitro mouse lymphoma forward gene mutation assay resulted in mutations in the presence and absence of exogenous metabolic activation. The in vitro bacterial reverse gene mutation (Ames) assay, in vitro human lymphocyte chromosomal aberration assay, and an in vivo rat bone marrow cytogenetic assay did not demonstrate evidence of mutagenicity or clastogenicity.
Impairment of Fertility
Studies to determine if cisatracurium besylate impacts fertility have not been completed.

14 CLINICAL STUDIES

14.1 Skeletal Muscle Relaxation for Intubation of Adult Patients

The efficacy of cisatracurium to provide skeletal muscle relaxation to facilitate tracheal intubation during surgery was established in six studies in adult patients. In all these studies patients had general anesthesia and mechanical ventilation.

- Cisatracurium doses between 0.15 and 0.2 mg/kg were evaluated in 240 adults. Maximum neuromuscular blockade generally occurred in within 4 minutes for this dose range.
- When administered during induction using thiopental or propofol and co-induction agents (i.e., fentanyl and midazolam), excellent to good intubating conditions were generally achieved within 2 minutes (excellent intubation conditions most frequently achieved with the 0.2 mg/kg dose of cisatracurium).
- Following the induction of general anesthesia with propofol, nitrous oxide/oxygen, and co-induction agents (e.g., fentanyl and midazolam), good or excellent conditions for tracheal intubation occurred in 96/102 (94%) patients in 1.5 to 2 minutes following cisatracurium doses of 0.15 mg/kg and in 97/110 (88%) patients in 1.5 minutes following cisatracurium doses of 0.2 mg/kg.

In Study 1, the clinically effective duration of action for 0.15 and 0.2 mg/kg cisatracurium using propofol anesthesia was 55 minutes (range: 44 to 74 minutes) and 61 minutes (range: 41 to 81 minutes), respectively.
In Studies 2 and 3, cisatracurium doses of 0.25 and 0.4 mg/kg were evaluated in 30 patients under opioid/nitrous oxide/oxygen anesthesia and provided 78 (66 to 86) and 91 (59 to 107) minutes of clinical relaxation, respectively.
In Study 4, two minutes after fentanyl and midazolam were administered, patients received thiopental anesthesia. Intubating conditions were assessed at 120 seconds following administration of 0.15 mg/kg or 0.2 mg/kg of cisatracurium in 51 patients (see Table 11).

Table 11. Intubating Conditions at 120 Seconds after Cisatracurium Administration with Thiopental Anesthesia in Adult Surgery Patients in Study 4
 | Cisatracurium 0.15 mg/kg (n = 26) | Cisatracurium 0.20 mg/kg (n = 25)
Excellent and Good | 88% | 96%
95% CI | 76,100 | 88,100
Excellent | 31% | 60%
Good | 58% | 36%
*Excellent: Easy passage of tube without coughing. Vocal cords relaxed and abducted.
Good: Passage of tube with slight coughing and/or bucking. Vocal cords relaxed and abducted.

Excellent intubating conditions were more frequently achieved with the 0.2 mg/kg dose (60%) than the 0.15 mg/kg dose (31%) when intubation was attempted 120 seconds following cisatracurium.
Study 5 evaluated intubating conditions after 3 and 4 × ED95(0.15 mg/kg and 0.20 mg/kg) following induction with fentanyl and midazolam and either thiopental or propofol anesthesia. This study compared intubation conditions produced by these doses of cisatracurium after 90 seconds. Table 12 displays these results.

Table 12. Intubating Conditions at 90 Seconds after Cisatracurium Administration with Thiopental or Propofol Anesthesia in Study 5
Intubating Condition | Cisatracurium 0.15 mg/kg with Propofol (n = 31) | Cisatracurium 0.15 mg/kg with Thiopental (n = 31) | Cisatracurium 0.20 mg/kg with Propofol (n = 30) | Cisatracurium 0.20 mg/kg with Thiopental (n = 28)
Excellent and Good | 94% | 90% | 93% | 96%
95% CI | 85,100 | 80,100 | 84,100 | 90,100
Excellent | 58% | 55% | 70% | 57%
Good | 35% | 35% | 20% | 39%
* Excellent: Easy passage of tube without coughing. Vocal cords relaxed and abducted.
Good: Passage of tube with slight coughing and/or bucking. Vocal cords relaxed and abducted.

Excellent intubating conditions were more frequently observed with the 0.2 mg/kg dose when intubation was attempted 90 seconds following cisatracurium.

14.2 Skeletal Muscle Relaxation for Intubation of Pediatric Patients

The efficacy of cisatracurium to provide skeletal muscle relaxation to facilitate tracheal intubation was established in studies in pediatric patients aged 1 month to 12 years old. In these studies, patients had general anesthesia and mechanical ventilation.
In Study 6, a cisatracurium dose of 0.1 mg/kg was evaluated in 16 pediatric patients (ages 2 years to 12 years) during opioid anesthesia. When administered during stable opioid/nitrous oxide/oxygen anesthesia, maximum neuromuscular blockade was achieved in an average of 2.8 minutes (range: 1.8 to 6.7 minutes) with a clinically effective block for 28 minutes (range: 21 to 38 minutes).
In Study 7, a cisatracurium dose of 0.15 mg/kg was evaluated in 50 pediatric patients (ages 1 month to 12 years) during opioid anesthesia. When administered during stable opioid/nitrous oxide/oxygen anesthesia, maximum neuromuscular blockade was achieved in an average of about 3 minutes (range: 1.5 to 8 minutes) with a clinically effective block for 36 minutes (range: 29 to 46 minutes) in 24 patients ages 2 to 12 years. In 27 infants (1 to 23 months), maximum neuromuscular block was achieved in about 2 minutes (range: 1.3 to 4.3 minutes) with a clinically effective block for about 43 minutes (range: 34 to 58 minutes) with this dose.
Study 7 also evaluated intubating conditions in 180 pediatric patients (ages 1 month to 12 years) after administration of cisatracurium doses of 0.15 mg/kg following induction with either halothane (with halothane/nitrous oxide/oxygen maintenance) or thiopentone and fentanyl (with thiopentone/fentanyl nitrous oxide/oxygen maintenance). Table 13 displays the intubating conditions by type of anesthesia, and pediatric age group. Excellent or good intubating conditions were produced 120 seconds following 0.15 mg/kg of cisatracurium in 88/90 (98%) of patients induced with halothane and in 85/90 (94%) of patients induced with thiopentone and fentanyl. There were no patients for whom intubation was not possible, but there were 7/120 patients aged 1 year to 12 years old for whom intubating conditions were described as poor.

Table 13. Intubating Conditions at 120 Seconds* in Pediatric Patients Ages 1 Month to 12 Years Old in Study 7
 | Cisatracurium 0.15 mg/kg 1 to 11 mo. |  | Cisatracurium 0.15 mg/kg 1 to 4 years |  | Cisatracurium 0.15 mg/kg 5 to 12 years
 | Halothane Anesthesia (n = 30) | Thiopentone/ Fentanyl Anesthesia (n = 30) | Halothane Anesthesia (n = 30) | Thiopentone/ Fentanyl Anesthesia (n = 30) | Halothane Anesthesia (n = 30) | Thiopentone/ Fentanyl Anesthesia (n = 30)
Excellent and Good | 100% | 100% | 97% | 87% | 97% | 97%
Excellent | 100% | 83% | 90% | 63% | 73% | 70%
Good | 0% | 17% | 7% | 23% | 23% | 27%
Poor | 0% | 0% | 3% | 13% | 3% | 3%
*Excellent: Easy passage of the tube without coughing. Vocal cords relaxed and abducted.
Good: Passage of tube with slight coughing and/or bucking. Vocal cords relaxed and abducted.
Poor: Passage of tube with moderate coughing and/or bucking. Vocal cords moderately adducted. Response of patient requires adjustment of ventilation pressure and/or rate.

14.3 Skeletal Muscle Relaxation in ICU Patients

Long-term infusion (up to 6 days) of cisatracurium during mechanical ventilation in the ICU was evaluated in two studies.
Study 8 was a randomized, double-blind study using presence of a single twitch during train-of-four (TOF) monitoring to regulate dosage. Patients treated with cisatracurium (n = 19) recovered neuromuscular function (T4:T1 ratio ≥ 70%) following termination of infusion in approximately 55 minutes (range: 20 to 270).
In Study 9, cisatracurium patients recovered neuromuscular function in approximately 50 minutes (range: 20 to 175; n = 34).

16 HOW SUPPLIED/STORAGE AND HANDLING

Cisatracurium besylate injection, USP is a clear colorless to slightly yellow or greenish-yellow solution and is supplied as follows:

10 mg per 5 mL (2 mg/mL)

5 mL Single-Dose Vials

in a carton of 10 NDC 55150-284-10

Does not contain benzyl alcohol.

Discard unused portion of the 5 mL single-dose vials.

20 mg per 10 mL (2 mg/mL)

10 mL Multiple-Dose Vials

in a carton of 10 NDC 55150-286-10

Contains 0.9% w/v benzyl alcohol [see Warnings and Precautions (5.2)]

Storage

Refrigerate cisatracurium besylate injection, USP at 2°C to 8°C (36°F to 46°F) in the carton to preserve potency. Protect from light. DO NOT FREEZE. Upon removal of the unused vial from refrigeration to room temperature storage conditions (25°C/77°F), use cisatracurium besylate injection, USP within 21 days even if re-refrigerated.

The vial stoppers are not made with natural rubber latex.

17 PATIENT COUNSELING INFORMATION

Hypersensitivity Reactions Including Anaphylaxis
Advise the caregiver and/or family that severe hypersensitivity reactions have occurred with cisatracurium [see Warnings and Precautions (5.4)].
Distributed by:
Eugia US LLC
279 Princeton-Hightstown Rd.
E. Windsor, NJ 08520
Manufactured by:
Eugia Pharma Specialities Limited
Hyderabad – 500032
India

PACKAGE LABEL-PRINCIPAL DISPLAY PANEL - 20 mg per 10 mL (2 mg per mL) - Container Label

Rx only NDC 55150-286-01
Cisatracurium
Besylate
Injection, USP
20 mg per 10 mL*
(2 mg per mL)
WARNING: Paralyzing Agent
For Intravenous Injection
0.9% benzyl alcohol
(added as a preservative)
10 mL Multiple-Dose Vial

PACKAGE LABEL-PRINCIPAL DISPLAY PANEL - 20 mg per 10 mL (2 mg per mL) - Container-Carton (10 Vials)

Rx only NDC 55150-286-10
Cisatracurium
Besylate
Injection, USP
20 mg per 10 mL*
(2 mg per mL)
WARNING: Paralyzing Agent
For Intravenous Injection
0.9% benzyl alcohol
(added as a preservative)
10 x 10 mL
eugia Multiple-Dose Vials

PACKAGE LABEL-PRINCIPAL DISPLAY PANEL - 2 mg/mL - Peel-off Sticker Label

Strength:____________ mg/mL Peel off & apply to syringe
Cisatracurium Besylate Injection, USP
Dt:__________ Tm:__________ By:__________ P1416958

PACKAGE LABEL-PRINCIPAL DISPLAY PANEL - 10 mg (base) / 5 mL (2 mg / mL) - Container Label

Rx only NDC 55150-284-01
Cisatracurium
Besylate
Injection, USP
10 mg (base) / 5 mL
(2 mg / mL)
WARNING: Paralyzing Agent
For Intravenous Injection
5 mL Single-Dose Vial

PACKAGE LABEL-PRINCIPAL DISPLAY PANEL - 10 mg per 5 mL (2 mg per mL) - Container-Carton (10 Vials)

Rx only NDC 55150-284-10
Cisatracurium
Besylate
Injection, USP
10 mg per 5 mL*
(2 mg per mL)
WARNING: Paralyzing Agent
For Intravenous Injection
Preservative Free
10 x 5 mL
eugia Single-Dose Vials

PACKAGE LABEL-PRINCIPAL DISPLAY PANEL - 2mg/mL - Peel-off Label

Strength:___________ mg/mL Peel off & apply to syringe
Cisatracurium Besylate Injection, USP
Dt:__________ Tm:__________ By:_________ P1416958